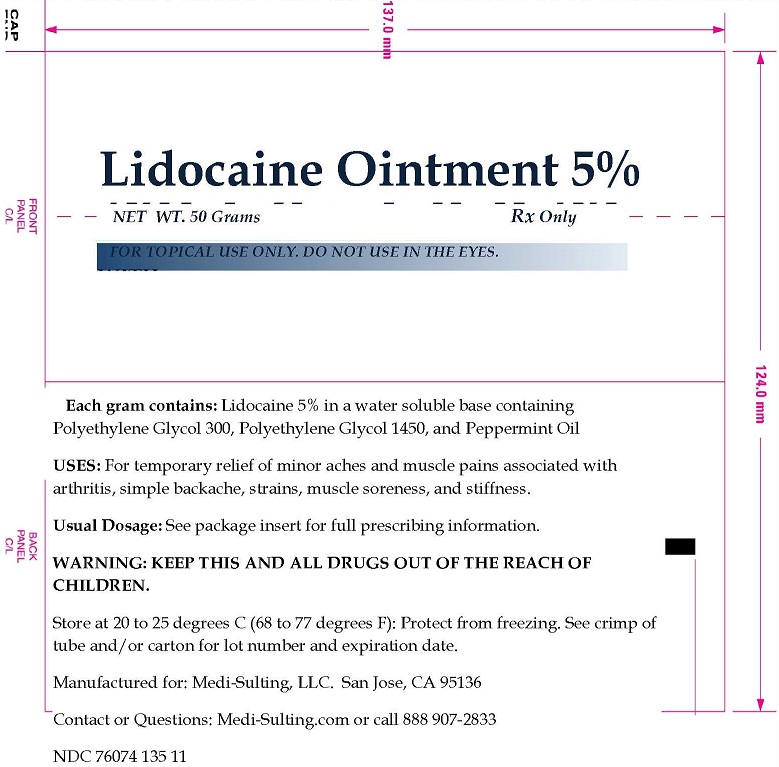 DRUG LABEL: LIDOCAINE
NDC: 76074-135 | Form: OINTMENT
Manufacturer: Two Hip Consulting, LLC
Category: prescription | Type: HUMAN PRESCRIPTION DRUG LABEL
Date: 20190206

ACTIVE INGREDIENTS: LIDOCAINE 5 g/100 g
INACTIVE INGREDIENTS: POLYETHYLENE GLYCOL 300; POLYETHYLENE GLYCOL 1450; PEPPERMINT OIL

INDICATIONS AND USAGE

USES: For temporary relief of minor aches and muscle pains associated with arthritis, simple backache, strains, muscle soreness, and stiffness.

WARNINGS

WARNING: KEEP THIS AND ALL DRUGS OUT OF THE REACH OF CHILDREN

OTHER SAFETY INFORMATION

Store at 20 to 25 degrees C (68 to 77 degrees F): Protect from freezing. See crimp of tube and/or carton for lot number and expiration date.